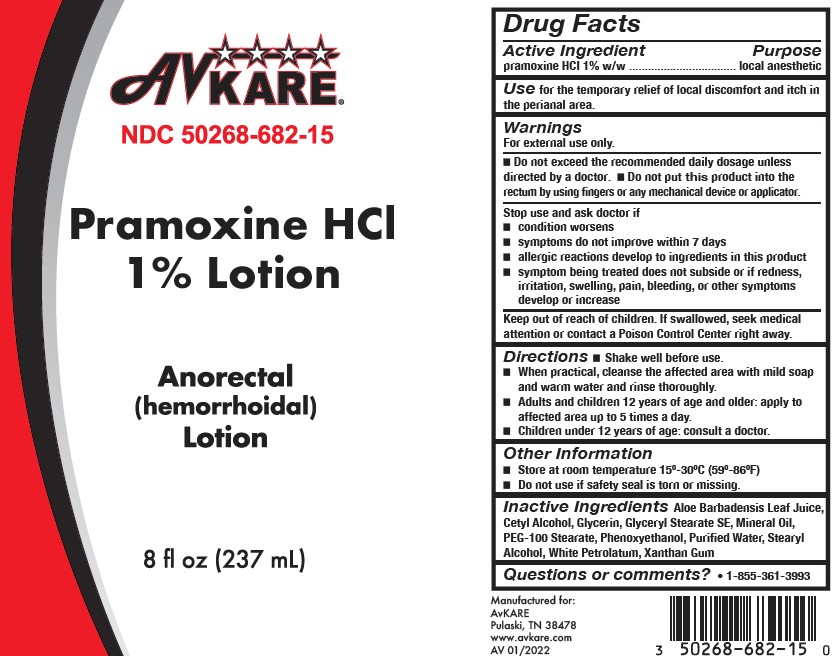 DRUG LABEL: PRAX
NDC: 50268-682 | Form: LOTION
Manufacturer: AvPAK
Category: otc | Type: HUMAN OTC DRUG LABEL
Date: 20240306

ACTIVE INGREDIENTS: PRAMOXINE HYDROCHLORIDE 10 mg/1 mL
INACTIVE INGREDIENTS: CETYL ALCOHOL; GLYCERIN; PETROLATUM; STEARYL ALCOHOL; MINERAL OIL; WATER; PHENOXYETHANOL; GLYCERYL STEARATE SE; XANTHAN GUM; PEG-100 STEARATE; ALOE VERA LEAF

Pramoxine HCl 1% Lotion

Active Ingredient

pramoxine HCl 1% w/w

Purpose

local anesthetic

Use

for the temporary relief of discomfort and itch in the perianal area

Warnings

For external use only.

Do not

- exceed the recommended daily dosage unless directed by a doctor
- put this product into the rectum by using fingers or any mechanical device or applicator

Stop use and ask a doctor if

- condition worsens
- symptoms do not improve within 7 days
- allergic reactions develop to ingredients in this product
- symptom being treated does not subside or if redness, irritation, swelling, pain, bleeding, or other symptoms develop or increase

Keep out of reach of children.

If swallowed, seek medical attention or contact a Poison Control Center right away.

Directions

- Shake well before use.
- When practical, cleanse the affected area with mild soap and warm water and rinse thoroughly.
- Adults and children 12 years of age and older: apply to affected area up to 5 times daily.
- Children under 12 years of age: consult a doctor.

Inactive Ingredients

Aloe Barbadensis Leaf Juice, Cetyl Alcohol, Glycerin, Glyceryl Stearate SE, Mineral Oil, PEG-100 Stearate, Phenoxyethanol, Purified Water, Stearyl Alcohol, White Petrolatum, Xanthan Gum

Package Label

Questions or comments call 1-855-361-3993.

Manufactured for:

AvKARE

Pulaski, TN 38478

www.avkare.com

AV 01/2022